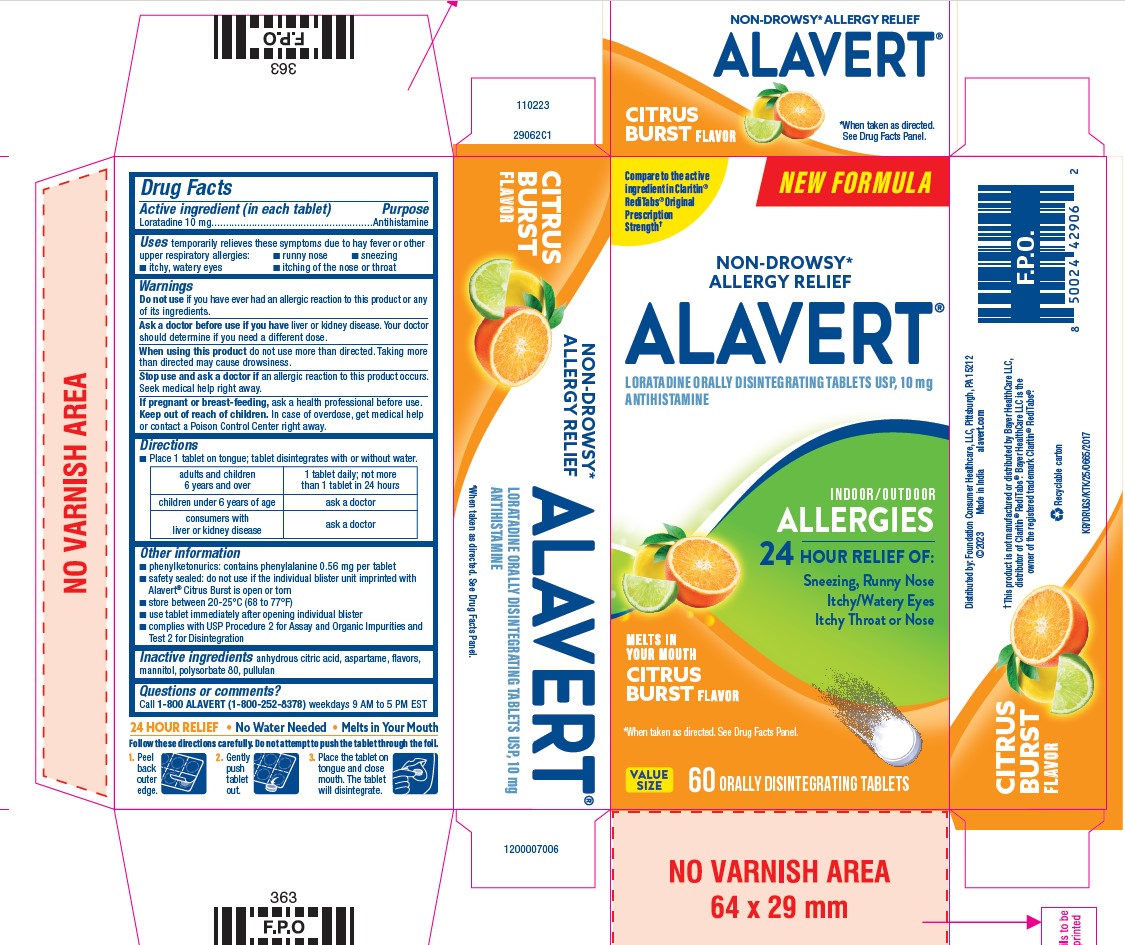 DRUG LABEL: Alavert
NDC: 69536-195 | Form: TABLET, ORALLY DISINTEGRATING
Manufacturer: Foundation Consumer Healthcare
Category: otc | Type: HUMAN OTC DRUG LABEL
Date: 20240624

ACTIVE INGREDIENTS: LORATADINE 10 mg/1 1
INACTIVE INGREDIENTS: ANHYDROUS CITRIC ACID; ASPARTAME; PULLULAN; POLYSORBATE 80; MANNITOL

Alavert®
Allergy Citrus Burst Flavor

Drug Facts

Active ingredient (in each tablet)

Loratadine 10 mg

Purpose

Antihistamine

Uses

temporarily relieves these symptoms due to hay fever or other upper respiratory allergies:

- runny nose
- sneezing
- itchy, watery eyes
- itching of the nose or throat

Warnings

Do not use if you have ever had an allergic reaction to this product or any of its ingredients

Ask a doctor before use if you have liver or kidney disease. Your doctor should determine if you need a different dose.

When using this product do not use more than directed. Taking more than recommended may cause drowsiness.

Stop use and ask a doctor if an allergic reaction to this product occurs. Seek medical help right away.

PREGNANCY OR BREAST FEEDING

If pregnant or breast-feeding, ask a health professional before use.

Keep out of reach of children. In case of overdose, get medical help or contact a Poison Control Center right away.

Directions

- Place 1 tablet on tongue; tablet disintegrates with or without water.

adults and children 6 years and over | 1 tablet daily; not more than 1 tablet in 24 hours
children under 6 years of age | ask a doctor
consumers with liver or kidney disease | ask a doctor

Other information

- phenylketonurics: contains phenylalanine 0.56 mg per tablet
- safety sealed: do not use if the individual blister unit imprinted with Alavert® Citrus Burst is open or torn
- store at 20-25°C (68-77°F)
- use tablet immediately after opening individual blister
- complies with USP procedure 2 for Assay and Organic Impurities and Test 2 for Disintegration

Inactive ingredients

anhydrous citric acid, aspartame, flavors, mannitol, polysorbate 80, pullulan

Questions or comments?

Call 1-800 ALAVERT (1-800-252-8378) weekdays 9 AM to 5 PM EST

Distributed by: Foundation Consumer Healthcare, LLC
Pittsburgh, PA 15212

PRINCIPAL DISPLAY PANEL - 60 Tablet Blister Pack Carton

NEW FORMULA

Compare to the active ingredient in Claritin ® RediTabs ® Original Prescription Strength †

NON-DROWSY*

ALLERGY RELIEF

ALAVERT ®

Loratadine Orally Disintegrating Tablet USP, 10 mg
Antihistamine

Indoor/Outdoor

ALLERGIES

24 Hour Relief of

Sneezing, Runny Nose

Itchy/Watery Eyes

Itchy Throat or Nose

Melts In Your Mouth

CITRUS BURST Flavor

*When taken as directed. See Drug Facts Panel.

VALUE SIZE 60 Orally Disintegrating Tablets